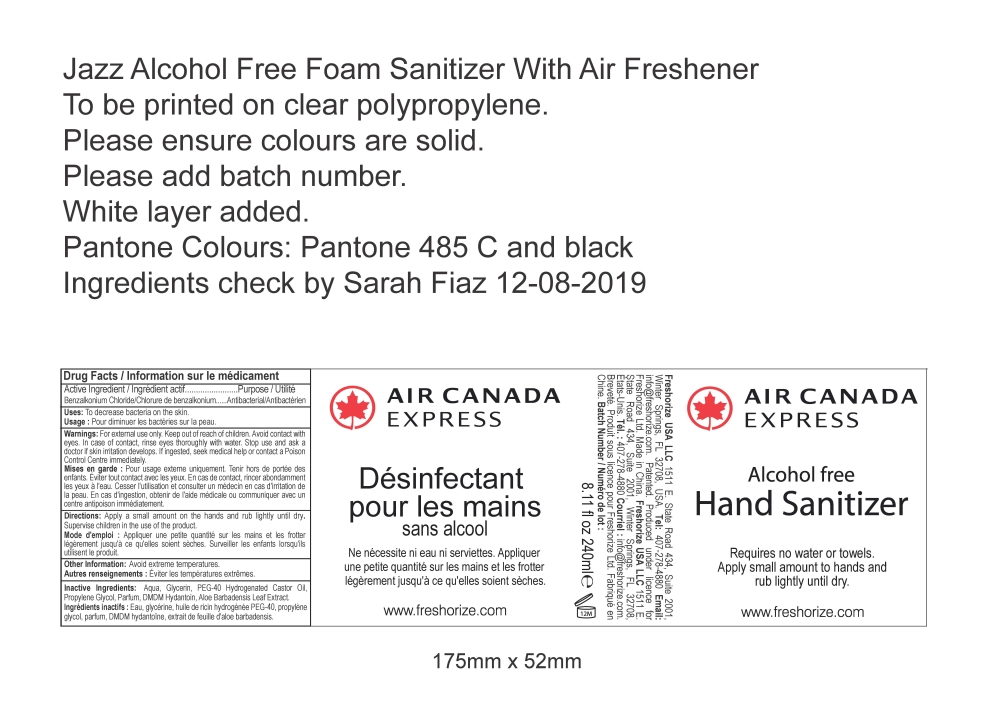 DRUG LABEL: Air Canada Foam Hand Sanitizer
NDC: 52305-603 | Form: LIQUID
Manufacturer: Freshorize Ltd
Category: otc | Type: HUMAN OTC DRUG LABEL
Date: 20201204

ACTIVE INGREDIENTS: BENZALKONIUM CHLORIDE 0.13 g/100 mL
INACTIVE INGREDIENTS: DMDM HYDANTOIN 0.2 g/100 mL; PROPYLENE 0.5 g/100 mL; HYDROGENATED CASTOR OIL 0.75 g/100 mL; ALOE VERA LEAF 0.1 g/100 mL; GLYCERIN 3 g/100 mL; WATER 95.07 g/100 mL

Air Canada Alcohol Free Foam Hand Sanitizer

Uses:

To decrease bacteria on the skin.

Warnings:

For external use only. Keep out of reach of children. Avoid contact with
eyes. In case of contact, rinse eyes thoroughly with water. Stop use and ask a
doctor if skin irritation develops. If ingested, seek medical help or contact a Poison
Control Centre immediately.

Warnings:

Keep out of reach of children.

Directions:

Apply a small amount on the hands and rub lightly until dry.
Supervise children in the use of the product.

Directions:

Apply a small amount on the hands and rub lightly until dry.

Other information:

Avoid extreme temperatures.

Inactive Ingredients:

Aqua, Glycerin, PEG-40 Hydrogenated Castor Oil,
Propylene Glycol, Parfum, DMDM Hydantoin, Aloe Barbadensis Leaf Extract.

Drug Facts:

Active Ingredient: Benzalkonium Chloride

Drug Facts

Purpose: Antibacterial